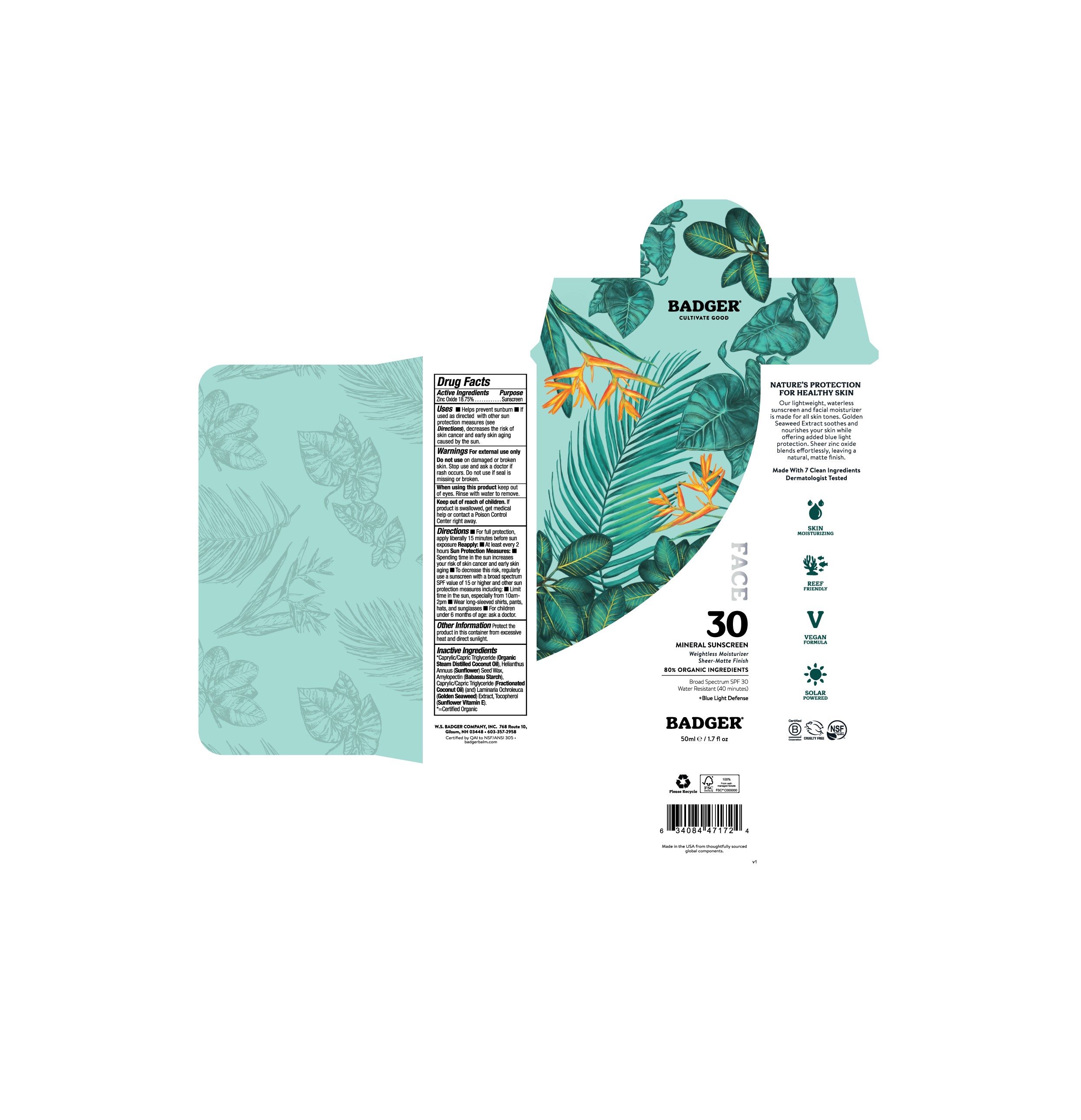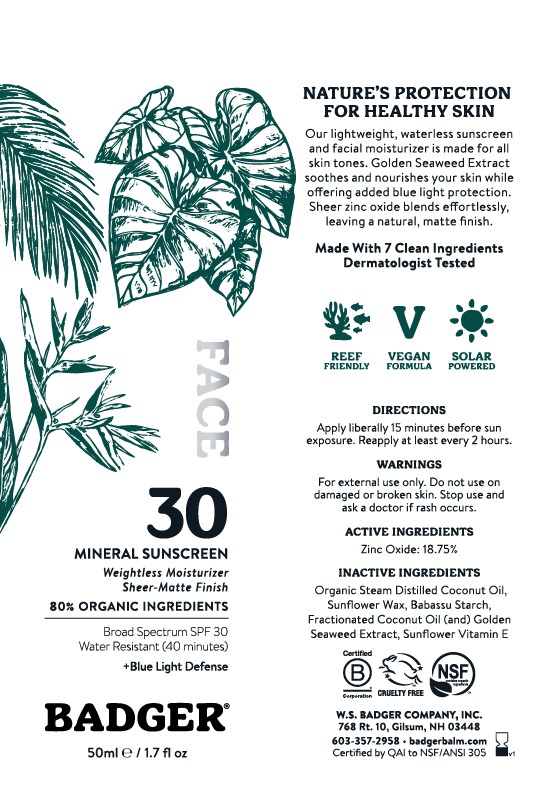 DRUG LABEL: Badger SPF 30 Daily Sunscreen
NDC: 62206-3061 | Form: CREAM
Manufacturer: W.S. Badger Company, Inc.
Category: otc | Type: HUMAN OTC DRUG LABEL
Date: 20241231

ACTIVE INGREDIENTS: ZINC OXIDE 18.75 g/100 mL
INACTIVE INGREDIENTS: MEDIUM-CHAIN TRIGLYCERIDES; AMYLOPECTIN, UNSPECIFIED SOURCE; LAMINARIA OCHROLEUCA; HELIANTHUS ANNUUS SEED WAX; TOCOPHEROL

Badger® SPF 30 Daily Mineral Sunscreen

Drug Facts

Active Ingredient

Uncoated Zinc Oxide 18.75%

Purpose

Sunscreen

Uses

- Helps prevent sunburn
- If used as directed with other sun protection measures (see Directions), decreases the risk of skin cancer and early skin aging caused by the sun.

Warnings

For external use only

Do not use on damaged or broken skin. Stop use and ask a doctor if rash occurs.

When using this product keep out of eyes. Rinse with water to remove.

Keep out of reach of children. If product is swallowed, get medical help or contact a Poison Control Center right away.

Directions

- For full protection, apply liberally15 minutes before sun exposure
- Use a water resistant sunscreen if swimming or sweating

Reapply:

- At least every 2 hours

Sun Protection Measures:

- Spending time in the sun increases your risk of skin cancer and early skin aging
- To decrease this risk, regularly use a sunscreen with a broad spectrum SPF value of 15 or higher and other sun protection measures including:
  - Limit time in the sun, especially from 10am-2pm
  - Wear long-sleeved shirts, pants, hats, and sunglasses
- For children under 6 months of age: ask a doctor.

Inactive Ingredients

[*=Certified Organic] , Amylopectin (Babassu Starch), Caprylic/Capric Triglyceride (and) Laminaria Ochroleuca (Golden Seaweed) Extract, Tocopherol (Sunflower Vitamin E).

Other Information

Protect the product in this container from excessive heat and direct sunlight.

Recent Major Changes

section heading: Uses

date change incorporated: 04/2024

section heading: Dosage and Administration

date change incorporated: 04/2024

PRINCIPAL DISPLAY PANEL - Box

BADGER ®

Mineral Sunscreen
Face

30

Weightless Moisturizer

Sheer-Matte Finish

80% Organic Ingredients

Broad Spectrum SPF 30

Water Resistant (40 minutes)

+Blue Light Defense
NATURE'S PROTECTION FOR HEALTHY SKIN

Our lightweight, waterless sunscreen and facial moisturizer is made for all skin tones. Golden Seaweed Extract soothes and nourishes your skin while offering added blue light protection. Sheer zinc oxide blends effortlessly, leaving a natural, mate finish.

Made with 6 Clean Ingredients

Dermatologist Tested

Reef Friendly

Vegan Formula

Solar Powered

NSF

Certified B Corporation

Cruelty Free

50ml / 1.7 fl oz